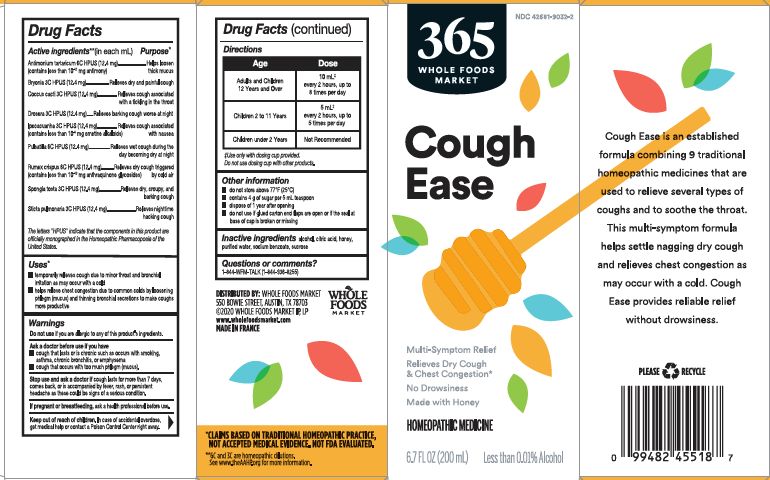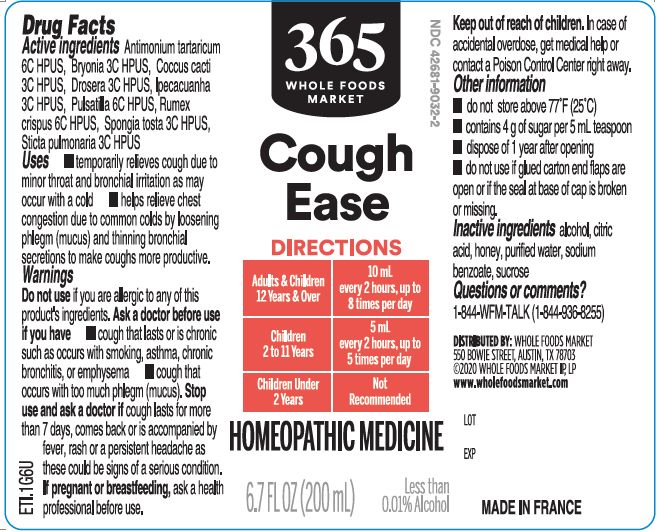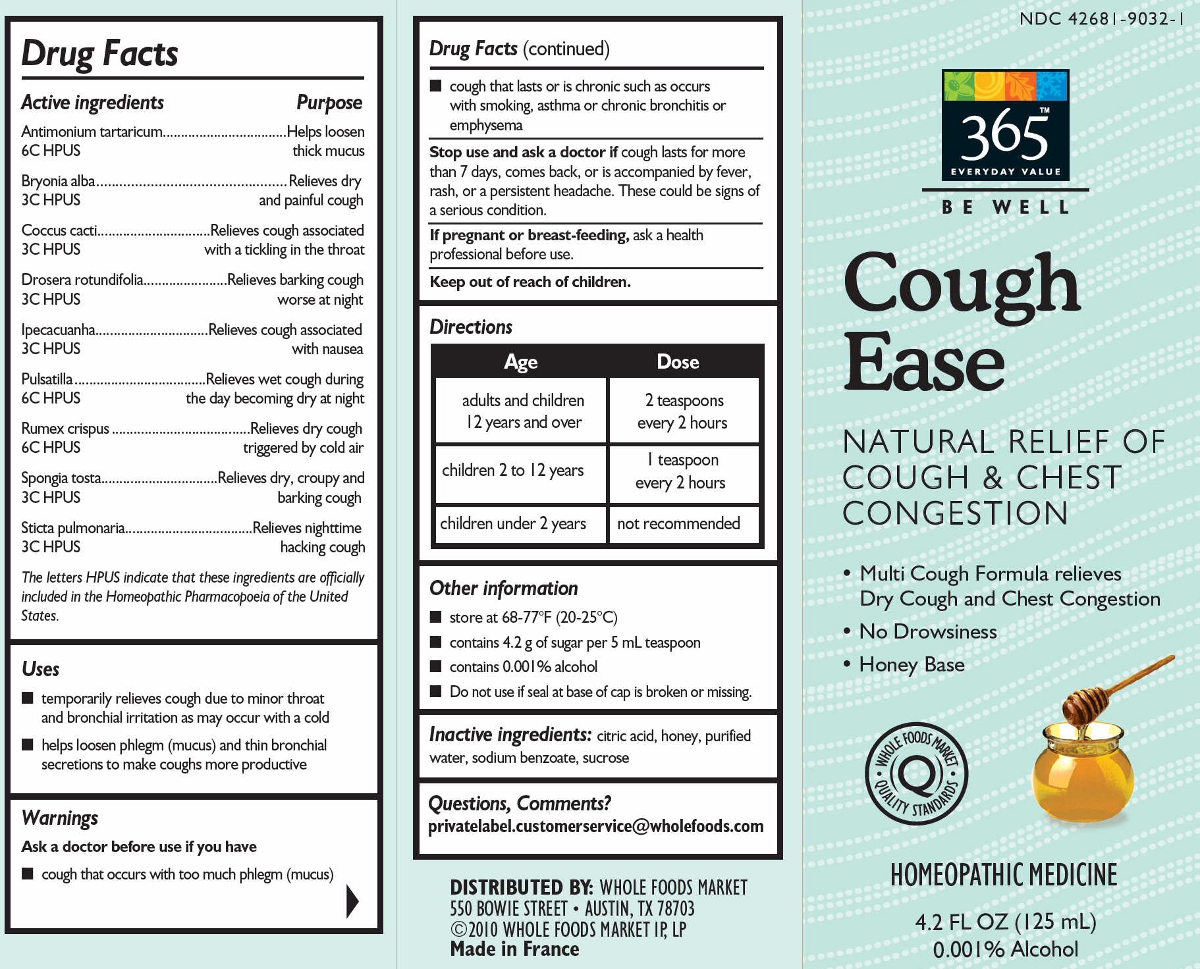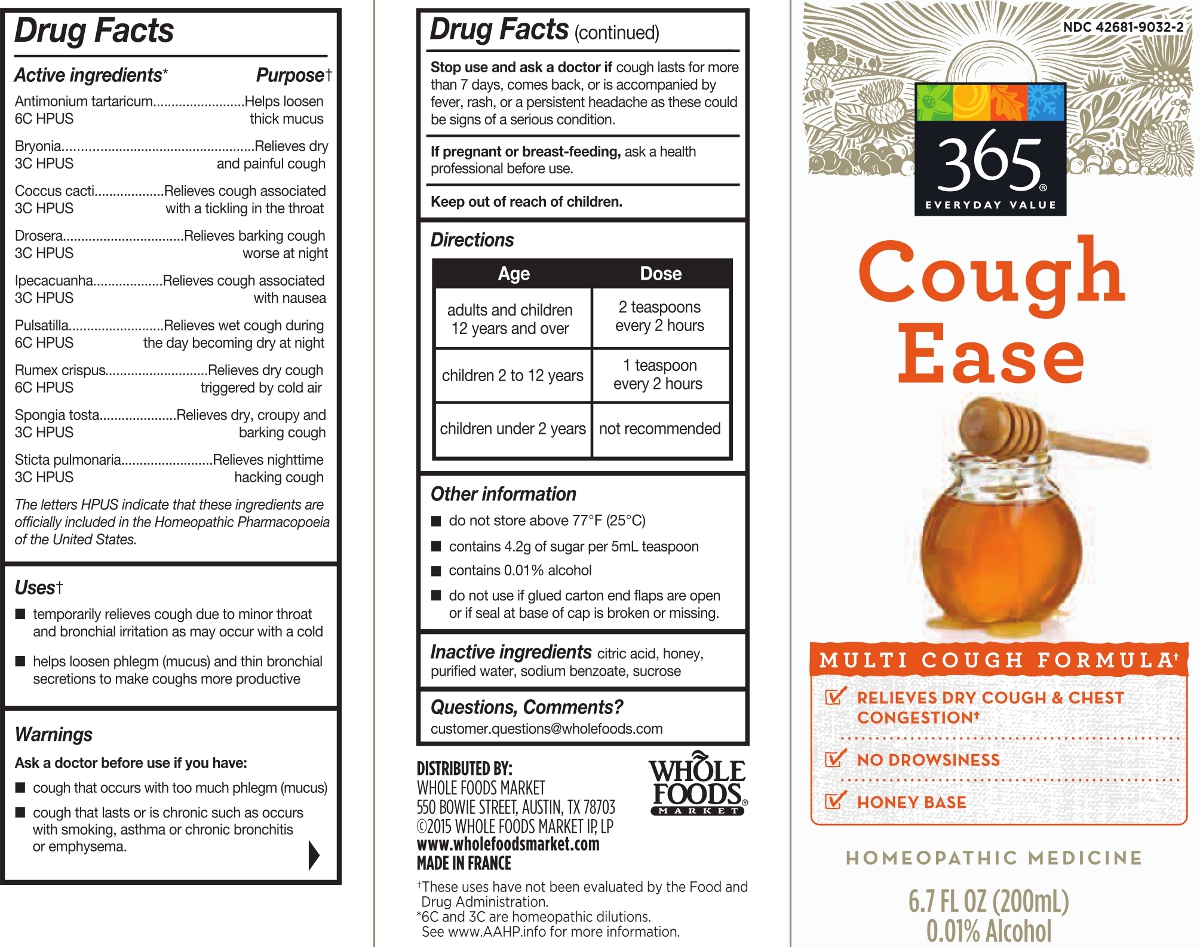 DRUG LABEL: 365 Everyday Value Be Well Cough Ease
NDC: 42681-9032 | Form: SYRUP
Manufacturer: WFM Private Label, LP
Category: homeopathic | Type: HUMAN OTC DRUG LABEL
Date: 20230316

ACTIVE INGREDIENTS: BRYONIA ALBA ROOT 3 [hp_C]/1 mL; PROTORTONIA CACTI 3 [hp_C]/1 mL; DROSERA ROTUNDIFOLIA 3 [hp_C]/1 mL; IPECAC 3 [hp_C]/1 mL; PULSATILLA VULGARIS 6 [hp_C]/1 mL; RUMEX CRISPUS ROOT 6 [hp_C]/1 mL; SPONGIA OFFICINALIS SKELETON, ROASTED 3 [hp_C]/1 mL; LOBARIA PULMONARIA 3 [hp_C]/1 mL; ANTIMONY POTASSIUM TARTRATE 6 [hp_C]/1 mL
INACTIVE INGREDIENTS: ALCOHOL; HONEY; SUCROSE; WATER; CITRIC ACID MONOHYDRATE; SODIUM BENZOATE

365 Everyday Value Cough Ease

ACTIVE INGREDIENT

Antimonium tartaricum 6C (12.4 mg) ** (contains less an 10^-11 mg antimony)
Bryonia alba 3C (12.4 mg)**
Coccus cacti 3C (12.4 mg)**
Drosera rotundifolia 3C (12.4 mg)**
Ipecacuanha 3C (12.4 mg)** (contains less than 10^-6 mg emetine alkaloids)
Pulsatilla 6C (12.4 mg)**
Rumex crispus 6C (12.4 mg)** (contains less than 10^-13 mg anthraquinone glycosides)
Spongia tosta 3C (12.4 mg)**
Sticta pulmonaria 3C (12.4 mg)**

(in each mL)

The letters "HPUS" indicate that the components in this product are officially monographed in the Homeopathic Pharmacopoeia of the United States.

PURPOSE

Antimonium tartaricum ... 6C Helps loosen thick mucus*
Bryonia alba 3C ... Relieves dry and painful cough*
Coccus cacti 3C ... Relieves cough associated with a tickling in the throat*
Drosera rotundifolia 3C ... Relieves barking cough worse at night*
Ipecacuanha 3C ... Relieves cough associated with nausea*
Pulsatilla 6C ... Relieves wet cough during the day becoming worse at night*
Rumex crispus 6C ... Relieves dry cough triggered by cold air*
Spongia tosta 3C ... Relieves dry, croupy and barking cough*
Sticta pulmonaria 3C ... Relieves nighttime hacking cough*

USES*

- temporary relieves cough due to minor throat and bronchial irritation as may occur with a cold
- helps relieve chest congestion due to common colds by loosening phlegm (mucus) and thinning bronchial secretions to make coughs more productive

Do not use if you are allergic to any of this product's ingredients.

Ask a doctor before use if you have

Cough that last or is chronic such as occurs with smoking, asthma, chronic bronchitis, or emphysema

Cough that occurs with too much phlegm (mucus)

Stop use and ask a doctor if cough lasts for more than 7 days, comes back, or is accompanied by fever, rash, or a persistent headache as these could be a signs of a serious condition.

PREGNANCY OR BREAST FEEDING

If pregnant or breast-feeding, ask a health professional before use.

Keep out of reach of children. In case of accidental overdose, get medical help or contact a Poison Control Center right away.

Directions

Adults and Children 12 Years and Over 10 mL ƚ every 2 hours, up to 8 times per day

Children 2 to 11 Years 5 mL ƚ every 2 hours, up to 5 times pers day

Children under 2 Years Not Recommended

ƚ Use only with dosing cup provided.

Do not use dosing cup with other products.

do not store above 77° F (25° C)

contains 4 g of sugar per 5 mL teaspoon

dispose of 1 year after opening

do not use if glued carton end flaps are open of if the seal at base of cap is broken or missing

Multi-Symptom Relief

Relieves Dry Cough & Chest Congestion*

No Drowsiness

Made with Honey

Homeopathic Medicine

6.7 FL OZ (200 mL)

Less than 0.01% Alcohol

*CLAIMS BASED ON TRADITIONAL HOMEOPATHIC PRACTICE, NOT ACCEPTED MEDICAL EVIDENCE. NOT FDA EVALUATED.
**6C and 3C are homeopathic dilutions. See www.theAAHP.org for more information.

INACTIVE INGREDIENT

alcohol, citric acid, honey, purified water, sodium benzoate, sucrose

Questions, Comments

1-844-WFM-TALK (1-844-936-8255)

Distributed by: Whole Foods Market

550 Bowie Street, Austin, TX 78703

©2020 Whole Foods Market IP, LP

www.wholefoodsmarket.com

Made in France

Principle Display Panel

Package images